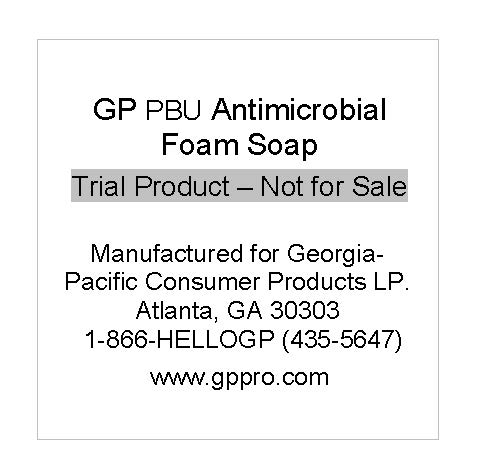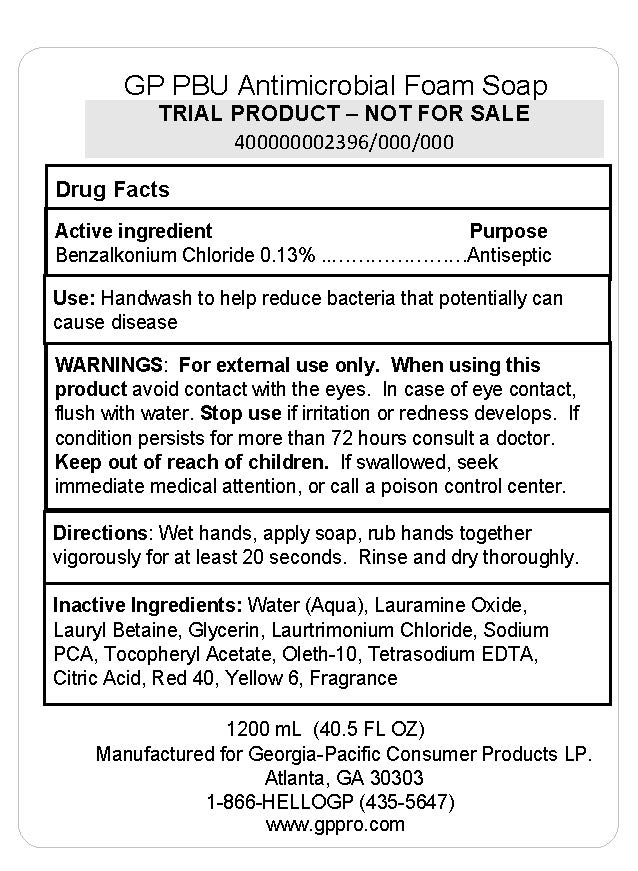 DRUG LABEL: GP PBU Antimicrobial Foam
NDC: 54622-313 | Form: SOLUTION
Manufacturer: Georgia Pacific Consumer Products
Category: otc | Type: HUMAN OTC DRUG LABEL
Date: 20240502

ACTIVE INGREDIENTS: BENZALKONIUM CHLORIDE 0.13 g/100 mL
INACTIVE INGREDIENTS: SODIUM PYRROLIDONE CARBOXYLATE; LAURAMINE OXIDE; LAURYL BETAINE; GLYCERIN; LAURTRIMONIUM CHLORIDE; EDETATE SODIUM; FD&C YELLOW NO. 6; OLETH-10; FD&C RED NO. 40; ANHYDROUS CITRIC ACID; WATER; .ALPHA.-TOCOPHEROL ACETATE

54622-313

Active ingredient

Benzalkonium chloride, 0.13%

Purpose

Antiseptic

Use

Handwash to help reduce bacteria that potentially can cause disease.

Warnings

For external use only

When using this product

Avoid contact with the eyes. In case of eye contact, flush with water.

Stop use

if irritation or redness developes. If condition persists for more than 72 hours consult a doctor.

Keep out of reach of children

If swallowed, seek immediate medical attention or call a poison control center.

Directions

Wet hands, apply soap, rub hands togetehr vigorously for at least 20 seconds.

Rinse and dry hands thoroughly.

Inactive ingredients

Water (Aqua), Lauramine Oxide, Lauryl Betaine, Glycerin, Laurtrimonium Chloride, Sodium PCA, Tocopheryl Acetate, Oleth-10, Tetrasodium EDTA, Citric Acid, Red 40, Yellow 6, Fragrance